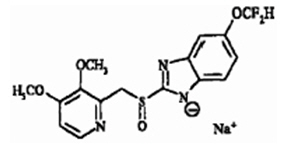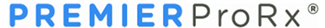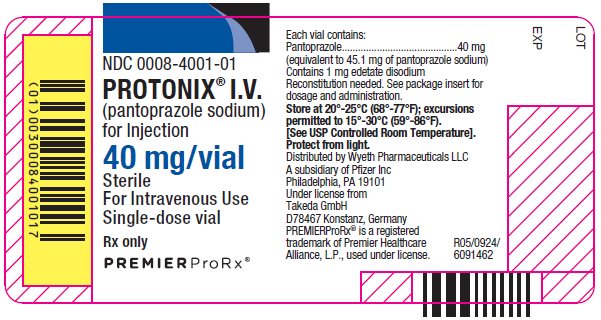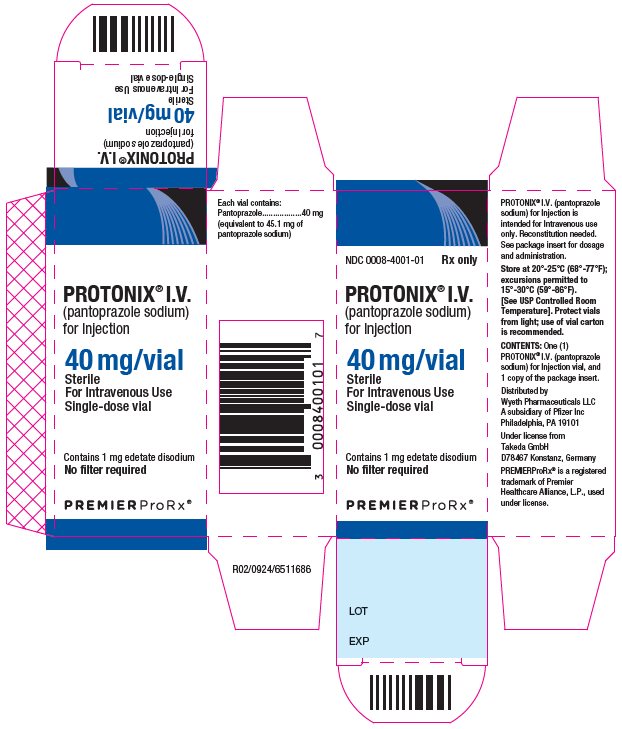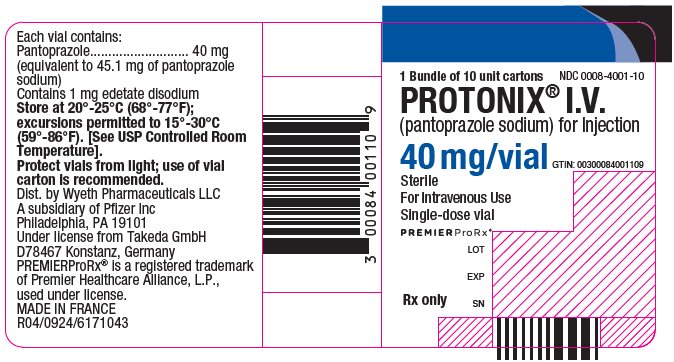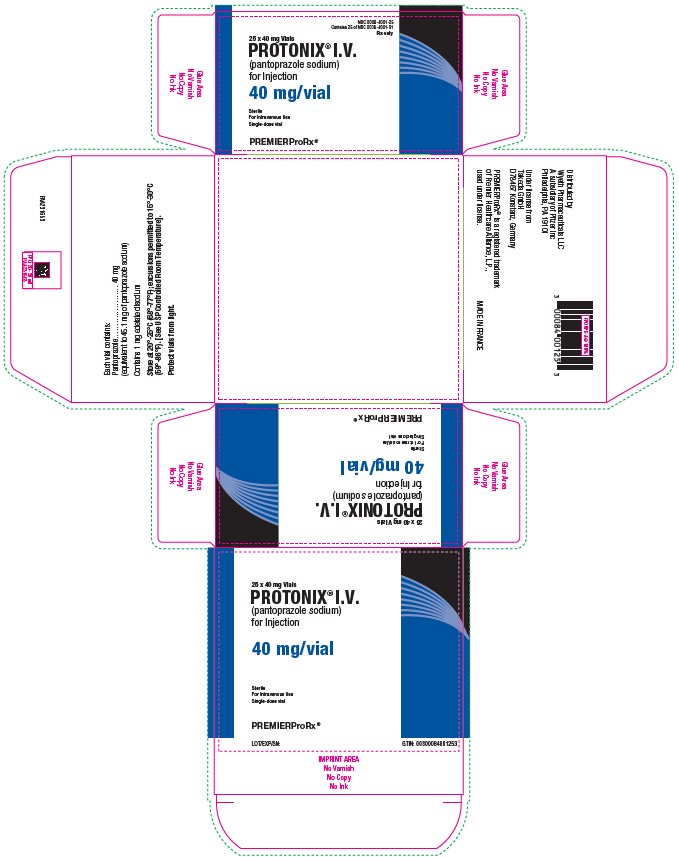 DRUG LABEL: Protonix
NDC: 0008-4001 | Form: INJECTION, POWDER, FOR SOLUTION
Manufacturer: Wyeth Pharmaceuticals LLC, a subsidiary of Pfizer Inc.
Category: prescription | Type: HUMAN PRESCRIPTION DRUG LABEL
Date: 20251222

ACTIVE INGREDIENTS: PANTOPRAZOLE SODIUM 40 mg/10 mL
INACTIVE INGREDIENTS: EDETATE DISODIUM 1 mg/10 mL; SODIUM HYDROXIDE

HIGHLIGHTS OF PRESCRIBING INFORMATION

These highlights do not include all the information needed to use PROTONIX I.V. safely and effectively. See full prescribing information for PROTONIX I.V.
PROTONIX® I.V. (pantoprazole sodium) for injection, for intravenous use
Initial U.S. approval: 2000

RECENT MAJOR CHANGES

Indications and Usage (1) | 8/2024
Dosage and Administration (2.1, 2.3) | 8/2024
Warnings and Precautions (5.2, 5.5) | 8/2024

1 INDICATIONS AND USAGE

PROTONIX I.V. is a proton pump inhibitor (PPI) indicated for treatment of:

- gastroesophageal reflux disease (GERD) and a history of erosive esophagitis (EE) for up to 10 days in adults and up to 7 days in pediatric patients 3 months and older. (1)
- pathological hypersecretion conditions including Zollinger-Ellison (ZE) Syndrome in adults. (1)

Limitations of Use

The safety and effectiveness of PROTONIX I.V. for the treatment of upper gastrointestinal bleeding have not been established in adult or pediatric patients. (1)

2 DOSAGE AND ADMINISTRATION

GERD and a History of EE

Adults:

- The recommended dosage is 40 mg once daily by intravenous injection (over at least 2 minutes) or intravenous infusion (for 15 minutes) for up to 10 days. (2.1)
- Discontinue as soon as the patient is able to receive oral treatment. Switch to an appropriate oral medication within 10 days of starting PROTONIX I.V. (2.1)

Pediatrics 3 Months of Age and Older:

- The recommended dosage for pediatric patients 3 months of age and older is based on age and actual body weight as shown in the table. (2.1)
- Administer as an intravenous infusion over 15 minutes once daily. (2.1)

Age and Body Weight |  | Recommended Dosage Regimen; (up to 7 days)
3 months to less than 1 year of age | Less than 12.5 kg | 0.8 mg/kg once daily
3 months to less than 1 year of age | 12.5 kg and above | 10 mg once daily
1 year to 17 years of age | Up to 15 kg | 10 mg once daily
1 year to 17 years of age | Greater than 15 kg; up to 40 kg | 20 mg once daily
1 year to 17 years of age | Greater than 40 kg | 40 mg once daily

- Discontinue PROTONIX I.V. as soon as the patient is able to tolerate oral treatment. Switch to an appropriate oral medication within 7 days of starting PROTONIX I.V. (2.1)

Pathological Hypersecretion Conditions, Including ZE Syndrome:

- The recommended adult dosage is 80 mg every 12 hours by intravenous injection (over at least 2 minutes) or intravenous infusion (for 15 minutes). (2.2)
- For information on how to adjust dosing for individual patient needs, see the full prescribing information. (2.2)
- When switching between intravenous to oral formulations of gastric acid inhibitors, consider the pharmacodynamic action of the drugs to ensure continuity of acid suppression. (2.2)
  Preparation and Administration Instructions
- See full prescribing information for preparation and administration instructions by indication. (2.3, 2.4)

3 DOSAGE FORMS AND STRENGTHS

For Injection: 40 mg pantoprazole freeze-dried powder in a single-dose vial for reconstitution or dilution. (3)

4 CONTRAINDICATIONS

- Known hypersensitivity to any component of the formulation or to substituted benzimidazoles. (4)
- Patients receiving rilpivirine-containing products. (4, 7)

5 WARNINGS AND PRECAUTIONS

- Gastric Malignancy: In adults, symptomatic response to therapy with PROTONIX I.V. does not preclude the presence of gastric malignancy. Consider additional follow-up and diagnostic testing. (5.1)
- Injection Site Reactions: Thrombophlebitis is associated with the administration of PROTONIX I.V. Assess the patient and remove the catheter if clinically indicated. (5.2)
- Potential Exacerbation of Zinc Deficiency: Consider zinc supplementation in patients who are prone to zinc deficiency. Caution should be used when other EDTA containing products are also co-administered intravenously. (5.3)
- Acute Tubulointerstitial Nephritis: Discontinue treatment and evaluate patients. (5.4)
- Clostridioides difficile-Associated Diarrhea: PPI therapy may be associated with increased risk. (5.5)
- Bone Fracture: Long-term and multiple daily dose PPI therapy may be associated with an increased risk for osteoporosis-related fractures of the hip, wrist or spine. (5.6)
- Severe Cutaneous Adverse Reactions: Discontinue at the first signs or symptoms of severe cutaneous adverse reactions or other signs of hypersensitivity and consider further evaluation. (5.7)
- Cutaneous and Systemic Lupus Erythematosus: Mostly cutaneous; new onset or exacerbation of existing disease; discontinue treatment and refer to specialist for evaluation. (5.8)
- Hepatic Effects: Elevations of transaminases observed. (5.9)
- Hypomagnesemia and Mineral Metabolism: Reported rarely with prolonged treatment with PPIs. (5.10)
- Fundic Gland Polyps: Risk increases with long-term use, especially beyond one year. Use the shortest duration of therapy. (5.11)

6 ADVERSE REACTIONS

Most common adverse reactions (>2%) are: headache, diarrhea, nausea, abdominal pain, vomiting, flatulence, dizziness, and arthralgia. (6.1)

To report SUSPECTED ADVERSE REACTIONS, contact Pfizer Inc. at 1-800-438-1985 or FDA at 1-800-FDA-1088 or www.fda.gov/medwatch.

7 DRUG INTERACTIONS

See the full prescribing information for a list of clinically important drug interactions. (7)

8 USE IN SPECIFIC POPULATIONS

Pregnancy: Based on animal data, may cause fetal harm. (8.1)

FULL PRESCRIBING INFORMATION

1 INDICATIONS AND USAGE

PROTONIX I.V. is indicated for treatment of:

- gastroesophageal reflux disease (GERD) and a history of erosive esophagitis (EE) for up to 10 days in adults and up to 7 days in pediatric patients 3 months and older.
- pathological hypersecretory conditions including Zollinger-Ellison (ZE) Syndrome in adults.

Limitations of Use

The safety and effectiveness of PROTONIX I.V. for the treatment of upper gastrointestinal bleeding have not been established in adult or pediatric patients.

2 DOSAGE AND ADMINISTRATION

2.1 Recommended Dosage for GERD Associated with a History of EE

Adult Patients

The recommended adult dosage of PROTONIX I.V. is 40 mg once daily by intravenous injection (over at least 2 minutes) or intravenous infusion (for 15 minutes) for up to 10 days. Discontinue PROTONIX I.V. as soon as the patient is able to tolerate oral treatment. Switch to an appropriate oral medication within 10 days of starting PROTONIX I.V.

Pediatric Patients

- The recommended dosage for pediatric patients 3 months of age and older is based on age and actual body weight as shown in Table 1 below.
- Administer as an intravenous infusion over 15 minutes once daily.

Table 1: Recommended Pediatric Dosage Regimen for GERD and a History of EE
Age and Body Weight |  | Recommended Dosage Regimen; (up to 7 days)
3 months to less than 1 year of age | Less than 12.5 kg | 0.8 mg/kg once daily
3 months to less than 1 year of age | 12.5 kg and above | 10 mg once daily
1 year to 17 years of age | Up to 15 kg | 10 mg once daily
1 year to 17 years of age | Greater than 15 kg; up to 40 kg | 20 mg once daily
1 year to 17 years of age | Greater than 40 kg | 40 mg once daily

- Discontinue PROTONIX I.V. as soon as the patient is able to tolerate oral treatment. Switch to an appropriate oral medication within 7 days of starting PROTONIX I.V.

2.2 Recommended Dosage for Pathological Hypersecretion Including Zollinger-Ellison Syndrome

- The recommended adult dosage of PROTONIX I.V. is 80 mg every 12 hours by intravenous injection (over at least 2 minutes) or intravenous infusion (for 15 minutes).
- Adjust the frequency of dosing to individual patient needs based on acid output measurements. In those patients who need a higher dosage, 80 mg intravenously every 8 hours is expected to maintain acid output below 10 mEq/h.
- When switching between intravenous to oral formulations of gastric acid inhibitors, consider the pharmacodynamic action of the drugs to ensure continuity of acid suppression.

2.3 Preparation and Administration Instructions for GERD Associated with a History of EE

15-Minute Intravenous Infusion for Pediatric or Adult Patients

1. Reconstitute each vial of PROTONIX I.V. with 10 mL of 0.9% Sodium Chloride Injection.

2. Dilute the resulting solution to a final concentration as described below:

- Pediatric patients 3 months to less than 1 year of age: Dilute with 21 mL 0.9% Sodium Chloride Injection to a final concentration of approximately 1.3 mg/mL.
- Pediatric patients 1 year to 17 years old and adult patients: Further dilute with 100 mL 5% Dextrose Injection or 0.9% Sodium Chloride Injection to a final concentration of approximately 0.4 mg/mL.

3. Inspect the diluted PROTONIX I.V. solution visually for particulate matter and discoloration prior to and during administration.

4. Withdraw the desired dose of the diluted PROTONIX I.V. solution for a pediatric or adult dose.

5. Discard any unused portion of the remaining PROTONIX I.V. solution.

6. Infuse intravenously over a period of approximately 15 minutes through a dedicated line or through a Y-site [see Dosage and Administration (2.5)].

7. Flush the intravenous line before and after administration of PROTONIX I.V. with either 5% Dextrose Injection or 0.9% Sodium Chloride Injection.

Storage

- Store the reconstituted solution may be up to 6 hours at room temperature up to 30°C (86°F) prior to further dilution.
- Store the diluted solution at room temperature up to 30°C (86°F) and must be used within 24 hours from the time of initial reconstitution.
- Do not freeze the reconstituted or diluted solution.

2-Minute Intravenous Injection for Adult Patients

1. Reconstitute each vial of PROTONIX I.V. with 10 mL of 0.9% Sodium Chloride Injection, to a final concentration of approximately 4 mg/mL.

2. Withdraw the dose of 40 mg of reconstituted PROTONIX I.V. solution.

3. Inspect the diluted PROTONIX I.V. solution visually for particulate matter and discoloration prior to and during administration.

4. Administer intravenously over a period of at least 2 minutes.

5. Flush the intravenous line before and after administration of PROTONIX I.V. with either 5% Dextrose Injection or 0.9% Sodium Chloride Injection.

Storage

- Store the reconstituted solution may be stored for up to 24 hours at room temperature up to 30°C (86°F) prior to intravenous infusion.
- Do not freeze the reconstituted solution.

2.4 Preparation and Administration Instructions for Pathological Hypersecretion Including Zollinger-Ellison Syndrome

15-Minute Intravenous Infusion

1. Reconstitute each vial of PROTONIX I.V. with 10 mL of 0.9% Sodium Chloride Injection.

2. Combine the contents of the two vials and dilute with 80 mL of 5% Dextrose Injection or Sodium Chloride Injection to a total volume of 100 mL with a final concentration of approximately 0.8 mg/mL.

3. Inspect the diluted PROTONIX I.V. solution visually for particulate matter and discoloration prior to and during administration.

4. Administer intravenously over a period of approximately 15 minutes at a rate of approximately 7 mL/min.

5. Flush the intravenous line before and after administration of PROTONIX I.V. with either 5% Dextrose Injection or 0.9% Sodium Chloride Injection.

Storage

- The reconstituted solution can be stored at room temperature up to 30°C (86°F) for up to 6 hours prior to further dilution.
- Once further diluted, the diluted solution can be stored at room temperature up to 30°C (86°F) for up to 24 hours from the time of initial reconstitution.
- Do not freeze the reconstituted or diluted solution.

2-Minute Intravenous Injection

1. Reconstitute each vial of PROTONIX I.V. with 10 mL of 0.9% Sodium Chloride Injection per vial to a final concentration of approximately 4 mg/mL.

2. Inspect the diluted PROTONIX I.V. solution visually for particulate matter and discoloration prior to and during administration.

3. Administer the total volume from both vials intravenously over a period of at least 2 minutes.

4. Flush the intravenous line before and after administration of PROTONIX I.V. with either 5% Dextrose Injection or 0.9% Sodium Chloride Injection.

Storage

- The reconstituted solution may be stored for up to 24 hours at room temperature.
- Do not freeze the reconstituted solution.

2.5 Compatibility Information

- Administer PROTONIX I.V. intravenously through a dedicated line or through a Y-site.
- When administering through a Y-site, PROTONIX I.V. is compatible with the following solutions:
  - 5% Dextrose Injection
  - 0.9% Sodium Chloride Injection
- Midazolam hydrochloride is incompatible with Y-site administration of PROTONIX I.V.
- PROTONIX I.V. may not be compatible with products containing zinc [see Warnings and Precautions (5.3)].
- Stop administering PROTONIX I.V. immediately through a Y-site if precipitation or discoloration occurs.

3 DOSAGE FORMS AND STRENGTHS

For Injection: 40 mg of pantoprazole white to off-white freeze-dried powder in a single-dose vial for reconstitution or dilution.

4 CONTRAINDICATIONS

- PROTONIX I.V. is contraindicated in patients with known hypersensitivity reactions including anaphylaxis to the formulation or any substituted benzimidazole. Hypersensitivity reactions may include anaphylaxis, anaphylactic shock, angioedema, bronchospasm, acute tubulointerstitial nephritis, and urticaria [see Warnings and Precautions (5.2, 5.4) and Adverse Reactions (6)].
- Proton pump inhibitors (PPIs), including PROTONIX I.V., are contraindicated in patients receiving rilpivirine-containing products [see Drug Interactions (7)].

5 WARNINGS AND PRECAUTIONS

5.1 Presence of Gastric Malignancy

In adults, symptomatic response to therapy with PROTONIX I.V. does not preclude the presence of gastric malignancy. Consider additional follow-up and diagnostic testing in adult patients who have a suboptimal response or an early symptomatic relapse after completing treatment with a PPI. In older patients, also consider an endoscopy.

5.2 Injection Site Reactions

Thrombophlebitis was associated with the administration of PROTONIX I.V. Assess the patient and remove the catheter if clinically indicated.

5.3 Potential for Exacerbation of Zinc Deficiency

PROTONIX I.V. contains edetate disodium (the salt form of EDTA), a chelator of metal ions including zinc. Therefore, zinc supplementation should be considered in patients treated with PROTONIX I.V. who are prone to zinc deficiency. Caution should be used when other EDTA containing products are also co-administered intravenously [see Dosage and Administration (2.5)].

5.4 Acute Tubulointerstitial Nephritis

Acute tubulointerstitial nephritis (TIN) has been observed in patients taking PPIs and may occur at any point during PPI therapy. Patients may present with varying signs and symptoms from symptomatic hypersensitivity reactions to non-specific symptoms of decreased renal function (e.g., malaise, nausea, anorexia). In reported case series, some patients were diagnosed on biopsy and in the absence of extra-renal manifestations (e.g., fever, rash or arthralgia). Discontinue PROTONIX I.V. and evaluate patients with suspected acute TIN [see Contraindications (4)].

5.5 Clostridioides difficile-Associated Diarrhea

Published observational studies suggest that PPI therapy like PROTONIX I.V. may be associated with an increased risk of Clostridioides difficile-associated diarrhea, especially in hospitalized patients. This diagnosis should be considered for diarrhea that does not improve [see Adverse Reactions (6.2)].

Patients should use the lowest dose and shortest duration of PPI therapy appropriate to the condition being treated.

5.6 Bone Fracture

Several published observational studies suggest that PPI therapy may be associated with an increased risk for osteoporosis-related fractures of the hip, wrist, or spine. The risk of fracture was increased in patients who received high-dose, defined as multiple daily doses, and long-term PPI therapy (a year or longer). Patients should use the lowest dose and shortest duration of PPI therapy appropriate to the condition being treated. Patients at risk for osteoporosis-related fractures should be managed according to established treatment guidelines [see Dosage and Administration (2.2, 2.4) and Adverse Reactions (6)].

5.7 Severe Cutaneous Adverse Reactions

Severe cutaneous adverse reactions, including erythema multiforme, Stevens-Johnson syndrome (SJS), toxic epidermal necrolysis (TEN), drug reaction with eosinophilia and systemic symptoms (DRESS), and acute generalized exanthematous pustulosis (AGEP) have been reported in association with the use of PPIs [see Adverse Reactions (6.2)]. Discontinue PROTONIX I.V. at the first signs or symptoms of severe cutaneous adverse reactions or other signs of hypersensitivity and consider further evaluation.

5.8 Cutaneous and Systemic Lupus Erythematosus

Cutaneous lupus erythematosus (CLE) and systemic lupus erythematosus (SLE) have been reported in patients taking PPIs, including pantoprazole sodium. These events have occurred as both new onset and an exacerbation of existing autoimmune disease. The majority of PPI-induced lupus erythematous cases were CLE.

The most common form of CLE reported in patients treated with PPIs was subacute CLE (SCLE) and occurred within weeks to years after continuous drug therapy in patients ranging from infants to the elderly. Generally, histological findings were observed without organ involvement.

Systemic lupus erythematosus (SLE) is less commonly reported than CLE in patients receiving PPIs. PPI associated SLE is usually milder than non-drug induced SLE. Onset of SLE typically occurred within days to years after initiating treatment primarily in patients ranging from young adults to the elderly. The majority of patients presented with rash; however, arthralgia and cytopenia were also reported.

Avoid administration of PPIs for longer than medically indicated. If signs or symptoms consistent with CLE or SLE are noted in patients receiving PROTONIX I.V., discontinue the drug and refer the patient to the appropriate specialist for evaluation. Most patients improve with discontinuation of the PPI alone in 4 to 12 weeks. Serological testing (e.g., ANA) may be positive and elevated serological test results may take longer to resolve than clinical manifestations.

5.9 Hepatic Effects

Mild, transient transaminase elevations have been observed in clinical studies. The clinical significance of this finding in a large population of subjects administered PROTONIX I.V. is unknown [see Adverse Reactions (6)].

5.10 Hypomagnesemia and Mineral Metabolism

Hypomagnesemia, symptomatic and asymptomatic, has been reported rarely in patients treated with PPIs for at least three months, and in most cases after a year of therapy. Serious adverse events include tetany, arrhythmias, and seizures. Hypomagnesemia may lead to hypocalcemia and/or hypokalemia and may exacerbate underlying hypocalcemia in at-risk patients. In most patients, treatment of hypomagnesemia required magnesium replacement and discontinuation of the PPI.

For patients expected to be on prolonged treatment or who take PPIs with medications such as digoxin or drugs that may cause hypomagnesemia (e.g., diuretics), health care professionals may consider monitoring magnesium levels prior to initiation of PPI treatment and periodically [see Adverse Reactions (6.2)].

Consider monitoring magnesium and calcium levels prior to initiation of PROTONIX I.V. and periodically while on treatment in patients with a preexisting risk of hypocalcemia (e.g., hypoparathyroidism). Supplement with magnesium and/or calcium as necessary. If hypocalcemia is refractory to treatment, consider discontinuing the PPI.

5.11 Fundic Gland Polyps

PPI use is associated with an increased risk of fundic gland polyps that increases with long-term use, especially beyond one year. Most PPI users who developed fundic gland polyps were asymptomatic and fundic gland polyps were identified incidentally on endoscopy. Use the shortest duration of PPI therapy appropriate to the condition being treated.

5.12 Interference with Investigations for Neuroendocrine Tumors

Serum chromogranin A (CgA) levels increase secondary to drug-induced decreases in gastric acidity. The increased CgA level may cause false positive results in diagnostic investigations for neuroendocrine tumors. Healthcare providers should temporarily stop PROTONIX I.V. treatment at least 14 days before assessing CgA levels and consider repeating the test if initial CgA levels are high. If serial tests are performed (e.g., for monitoring), the same commercial laboratory should be used for testing, as reference ranges between tests may vary [see Clinical Pharmacology (12.2)].

5.13 Interference with Urine Screen for THC

Pantoprazole sodium may produce false-positive urine screen for THC (tetrahydrocannabinol) [see Drug Interactions (7)].

5.14 Concomitant Use of PROTONIX I.V. with Methotrexate

Literature suggests that concomitant use of PPIs with methotrexate (primarily at high dose; see methotrexate prescribing information) may elevate and prolong serum levels of methotrexate and/or its metabolite, possibly leading to methotrexate toxicities. In high-dose methotrexate administration, a temporary withdrawal of the PPI may be considered in some patients [see Drug Interactions (7)].

6 ADVERSE REACTIONS

The following serious adverse reactions are described below and elsewhere in labeling:

- Injection Site Reactions [see Warnings and Precautions (5.2)]
- Potential for Exacerbation of Zinc Deficiency [see Warnings and Precautions (5.3)]
- Acute Tubulointerstitial Nephritis [see Warnings and Precautions (5.4)]
- Clostridioides difficile-Associated Diarrhea [see Warnings and Precautions (5.5)]
- Bone Fracture [see Warnings and Precautions (5.6)]
- Severe Cutaneous Adverse Reactions [see Warnings and Precautions (5.7)]
- Cutaneous and Systemic Lupus Erythematosus [see Warnings and Precautions (5.8)]
- Hepatic Effects [see Warnings and Precautions (5.9)]
- Hypomagnesemia and Mineral Metabolism [see Warnings and Precautions (5.10)]
- Fundic Gland Polyps [see Warnings and Precautions (5.11)]

6.1 Clinical Trials Experience

Because clinical trials are conducted under widely varying conditions, adverse reaction rates observed in the clinical trials of a drug cannot be directly compared to rates in the clinical trials of another drug and may not reflect the rates observed in clinical practice.

Gastroesophageal Reflux Disease (GERD)

Adults

Safety in nine randomized comparative US clinical trials in patients with GERD included 1,473 patients on oral pantoprazole (20 mg or 40 mg), 299 patients on an H2-receptor antagonist, 46 patients on another PPI, and 82 patients on placebo. The most frequently occurring adverse reactions are listed in Table 2.

The number of patients treated in comparative studies with PROTONIX I.V. is limited; however, the adverse reactions seen were similar to those seen in the oral studies. Thrombophlebitis was the only new adverse reaction identified with PROTONIX I.V.

Table 2: Adverse Reactions Reported in Clinical Trials of Adult Patients with GERD at a Frequency of >2%
 | Oral Pantoprazole Sodium (n=1473) % | Comparators (n=345) % | Placebo (n=82) %
Headache | 12.2 | 12.8 | 8.5
Diarrhea | 8.8 | 9.6 | 4.9
Nausea | 7.0 | 5.2 | 9.8
Abdominal pain | 6.2 | 4.1 | 6.1
Vomiting | 4.3 | 3.5 | 2.4
Flatulence | 3.9 | 2.9 | 3.7
Dizziness | 3.0 | 2.9 | 1.2
Arthralgia | 2.8 | 1.4 | 1.2

Additional adverse reactions that were reported for oral pantoprazole sodium in US clinical trials with a frequency of ≤2% are listed below by body system:

Body as a Whole: allergic reaction, fever, photosensitivity reaction, facial edema, thrombophlebitis (intravenous only)

Gastrointestinal: constipation, dry mouth, hepatitis

Hematologic: leukopenia (reported in ex-US clinical trials only), thrombocytopenia

Metabolic/Nutritional: elevated CPK (creatine phosphokinase), generalized edema, elevated triglycerides, liver function tests abnormal

Musculoskeletal: myalgia

Nervous: depression, vertigo

Skin and Appendages: urticaria, rash, pruritus

Special Senses: blurred vision

Pediatrics

Adverse reactions reported with single and multiple doses of PROTONIX I.V. in 18 hospitalized pediatric patients 1 to 16 years of age were generally similar to those reported in adults treated with intravenous or oral pantoprazole sodium and in pediatric patients treated with oral pantoprazole sodium in clinical trials. Additionally, upper respiratory tract infections in pediatric patients less than 16 years of age and otitis media in pediatric patients less than 1 year of age were reported with oral pantoprazole sodium.

Zollinger-Ellison (ZE) Syndrome

In clinical studies of ZE Syndrome, adverse reactions reported in 35 patients administered PROTONIX I.V. doses of 80 mg to 240 mg per day for up to 2 years were similar to those reported in adult patients with GERD.

6.2 Postmarketing Experience

The following adverse reactions have been identified during post approval use of pantoprazole sodium products. Because these reactions are reported voluntarily from a population of uncertain size, it is not always possible to reliably estimate their frequency or establish a causal relationship to drug exposure.

These adverse reactions are listed below by body system:

General disorders and administration conditions: asthenia, fatigue, malaise

Immune system disorders: anaphylaxis (including anaphylactic shock), systemic lupus erythematosus

Investigations: weight changes

Skin and subcutaneous tissue disorders: severe dermatologic reactions (some fatal), including erythema multiforme, SJS/TEN, DRESS, AGEP, angioedema (Quincke's edema) and cutaneous lupus erythematosus

Musculoskeletal disorders: rhabdomyolysis, bone fracture

Renal and genitourinary disorders: acute tubulointerstitial nephritis, erectile dysfunction

Hepatobiliary disorders: hepatocellular damage leading to jaundice and hepatic failure

Psychiatric disorder: hallucinations, confusion, insomnia, somnolence

Metabolism and nutritional disorders: hyponatremia, hypomagnesemia, hypocalcemia, hypokalemia

Infections and infestations: Clostridioides difficile-associated diarrhea

Hematologic: pancytopenia, agranulocytosis

Nervous: ageusia, dysgeusia

Gastrointestinal disorders: fundic gland polyps

7 DRUG INTERACTIONS

Table 3 includes drugs with clinically important drug interactions and interaction with diagnostics when administered concomitantly with PROTONIX I.V. and instructions for preventing or managing them.

Consult the labeling of concomitantly used drugs to obtain further information about interactions with PPIs.

Table 3: Clinically Relevant Interactions Affecting Drugs Co-Administered with PROTONIX I.V. and Interaction with Diagnostics
Antiretrovirals
Clinical Impact: | The effect of PPIs on antiretroviral drugs is variable. The clinical importance and the mechanisms behind these interactions are not always known.; - Decreased exposure of some antiretroviral drugs (e.g., rilpivirine atazanavir, and nelfinavir) when used concomitantly with pantoprazole may reduce antiviral effect and promote the development of drug resistance. - Increased exposure of other antiretroviral drugs (e.g., saquinavir) when used concomitantly with pantoprazole may increase toxicity of the antiretroviral drugs. - There are other antiretroviral drugs which do not result in clinically relevant interactions with pantoprazole.
Intervention: | Rilpivirine-containing products: Concomitant use with PROTONIX I.V. is contraindicated [see Contraindications (4)]. See prescribing information. Atazanavir: See prescribing information for atazanavir for dosing information. Nelfinavir: Avoid concomitant use with PROTONIX I.V. See prescribing information for nelfinavir. Saquinavir: See the prescribing information for saquinavir and monitor for potential saquinavir toxicities. Other antiretrovirals: See prescribing information.
Warfarin
Clinical Impact: | Increased INR and prothrombin time in patients receiving PPIs, including pantoprazole, and warfarin concomitantly. Increases in INR and prothrombin time may lead to abnormal bleeding and even death.
Intervention: | Monitor INR and prothrombin time. Dose adjustment of warfarin may be needed to maintain target INR range. See prescribing information for warfarin.
Clopidogrel
Clinical Impact: | Concomitant administration of pantoprazole and clopidogrel in healthy subjects had no clinically important effect on exposure to the active metabolite of clopidogrel or clopidogrel-induced platelet inhibition [see Clinical Pharmacology (12.3)].
Intervention: | No dose adjustment of clopidogrel is necessary when administered with an approved dose of PROTONIX I.V.
Methotrexate
Clinical Impact: | Concomitant use of PPIs with methotrexate (primarily at high dose) may elevate and prolong serum concentrations of methotrexate and/or its metabolite hydroxymethotrexate, possibly leading to methotrexate toxicities. No formal drug interaction studies of high-dose methotrexate with PPIs have been conducted [see Warnings and Precautions (5.14)].
Intervention: | A temporary withdrawal of PROTONIX I.V. may be considered in some patients receiving high-dose methotrexate.
Drugs Dependent on Gastric pH for Absorption (e.g., iron salts, erlotinib, dasatinib, nilotinib, mycophenolate mofetil, ketoconazole/itraconazole)
Clinical Impact: | Pantoprazole can reduce the absorption of other drugs due to its effect on reducing intragastric acidity.
Intervention: | Mycophenolate mofetil (MMF): Co-administration of pantoprazole sodium in healthy subjects and in transplant patients receiving MMF has been reported to reduce the exposure to the active metabolite, mycophenolic acid (MPA), possibly due to a decrease in MMF solubility at an increased gastric pH [see Clinical Pharmacology (12.3)]. The clinical relevance of reduced MPA exposure on organ rejection has not been established in transplant patients receiving PROTONIX I.V. and MMF. Use PROTONIX I.V. with caution in transplant patients receiving MMF. See the prescribing information for other drugs dependent on gastric pH for absorption.
Interactions with Investigations of Neuroendocrine Tumors
Clinical Impact: | CgA levels increase secondary to PPI-induced decreases in gastric acidity. The increased CgA level may cause false positive results in diagnostic investigations for neuroendocrine tumors [see Warnings and Precautions (5.12) and Clinical Pharmacology (12.2)].
Intervention: | Temporarily stop PROTONIX I.V. treatment at least 14 days before assessing CgA levels and consider repeating the test if initial CgA levels are high. If serial tests are performed (e.g., for monitoring), the same commercial laboratory should be used for testing, as reference ranges between tests may vary.
False Positive Urine Tests for THC
Clinical Impact: | There have been reports of false positive urine screening tests for tetrahydrocannabinol (THC) in patients receiving PPIs [see Warnings and Precautions (5.13)].
Intervention: | An alternative confirmatory method should be considered to verify positive results.

8 USE IN SPECIFIC POPULATIONS

8.1 Pregnancy

Risk Summary

Available data from published observational studies did not demonstrate an association of major malformations or other adverse pregnancy outcomes with pantoprazole.

In animal reproduction studies, no evidence of adverse development outcomes was observed with pantoprazole sodium. Reproduction studies have been performed in rats at intravenous doses up to 20 mg/kg/day (4 times the recommended human dose) and rabbits at intravenous doses up to 15 mg/kg/day (6 times the recommended human dose) with administration of pantoprazole during organogenesis in pregnant animals and have revealed no evidence of harm to the fetus due to pantoprazole in this study (see Data).

A pre-and post-natal development toxicity study in rats with additional endpoints to evaluate the effect on bone development was performed with pantoprazole sodium. Oral pantoprazole doses of 5, 15, and 30 mg/kg/day (approximately 1, 3, and 6 times the human dose of 40 mg/day) were administered to pregnant females from gestation day (GD) 6 through lactation day (LD) 21. Changes in bone morphology were observed in pups exposed to pantoprazole in utero and through milk during the period of lactation as well as by oral dosing from postnatal day (PND) 4 through PND 21 [see Use in Specific Populations (8.4)]. There were no drug-related findings in maternal animals. Advise pregnant women of the potential risk of fetal harm.

The estimated background risk of major birth defects and miscarriage for the indicated population is unknown. All pregnancies have a background risk of birth defect, loss or other adverse outcomes. In the U.S. general population, the estimated background risk of major birth defects and miscarriage in the clinically recognized pregnancies is 2 to 4% and 15 to 20%, respectively.

Data

Human Data

Available data from published observational studies failed to demonstrate an association of adverse pregnancy-related outcomes and pantoprazole use. Methodological limitations of these observational studies cannot definitely establish or exclude any drug-associated risk during pregnancy. In a prospective study by the European Network of Teratology Information Services, outcomes from a group of 53 pregnant women administered median daily doses of 40 mg pantoprazole were compared to a control group of 868 pregnant women who did not take any proton pump inhibitors (PPIs). There was no difference in the rate of major malformations between women exposed to PPIs and the control group, corresponding to a Relative Risk (RR)=0.55, [95% Confidence Interval (CI) 0.08–3.95]. In a population-based retrospective cohort study covering all live births in Denmark from 1996 to 2008, there was no significant increase in major birth defects during analysis of first trimester exposure to pantoprazole in 549 live births. A meta-analysis that compared 1,530 pregnant women exposed to PPIs in at least the first trimester with 133,410 unexposed pregnant women showed no significant increases in risk for congenital malformations or spontaneous abortion with exposure to PPIs (for major malformations OR=1.12 ([95% CI 0.86–1.45] and for spontaneous abortions OR=1.29 [95% CI 0.84–1.97]).

Animal Data

Reproduction studies have been performed in rats at intravenous pantoprazole doses up to 20 mg/kg/day (4 times the recommended human dose based on body surface area) and rabbits at intravenous doses up to 15 mg/kg/day (6 times the recommended human dose based on body surface area) with administration of pantoprazole sodium during organogenesis in pregnant animals and have revealed no evidence of impaired fertility or harm to the fetus due to pantoprazole.

A pre- and post-natal development toxicity study in rats with additional endpoints to evaluate the effect on bone development was performed with pantoprazole sodium. Oral pantoprazole doses of 5, 15, and 30 mg/kg/day (approximately 1, 3, and 6 times the human dose of 40 mg/day on a body surface area basis) were administered to pregnant females from gestation day (GD) 6 through lactation day (LD) 21. On postnatal day (PND 4) through PND 21, the pups were administered oral doses at 5, 15, and 30 mg/kg/day (approximately 1, 2.3, and 3.2 times the exposure (AUC) in humans at a dose of 40 mg). There were no drug-related findings in maternal animals. During the preweaning dosing phase (PND 4 to 21) of the pups, there were increased mortality and/or moribundity and decreased body weight and body weight gain at 5 mg/kg/day (approximately equal exposures (AUC) in humans receiving the 40 mg dose) and higher doses. On PND 21, decreased mean femur length and weight and changes in femur bone mass and geometry were observed in the offspring at 5 mg/kg/day (approximately equal exposures (AUC) in humans at the 40 mg dose) and higher doses. The femur findings included lower total area, bone mineral content and density, periosteal and endosteal circumference, and cross-sectional moment of inertia. There were no microscopic changes in the distal femur, proximal tibia, or stifle joints. Changes in bone parameters were partially reversible following a recovery period, with findings on PND 70 limited to lower femur metaphysis cortical/subcortical bone mineral density in female pups at 5 mg/kg/day (approximately equal exposures (AUC) in humans at the 40 mg dose) and higher doses.

8.2 Lactation

Risk Summary

The limited data from a single case report the presence of pantoprazole in human breast milk. There were no effects on the breastfed infant (see Data). There are no data on pantoprazole effects on milk production.

The developmental and health benefits of breastfeeding should be considered along with the mother's clinical need for PROTONIX I.V. and any potential adverse effects on the breastfed child from pantoprazole or from the underlying maternal condition.

Data

The breast milk of a 42-year-old woman receiving 40 mg of oral pantoprazole, at 10 months postpartum, was studied for 24 hours, to demonstrate low levels of pantoprazole present in the breast milk. Pantoprazole was detectable in milk only 2 and 4 hours after the dose with milk levels of approximately 36 mcg/L and 24 mcg/L, respectively. A milk-to-plasma ratio of 0.022 was observed at 2 hours after drug administration. Pantoprazole was not detectable (<10 mcg/L) in milk at 6, 8 and 24 hours after the dose. The relative dose to the infant was estimated to be 7.3 mcg of pantoprazole, which is equivalent to 0.14% of the weight-adjusted maternal dose. No adverse events in the infant were reported by the mother.

8.4 Pediatric Use

The safety and effectiveness of PROTONIX I.V. for the treatment of GERD and a history of EE for up to 7 days have been established in pediatric patients 3 months of age and older. Use of PROTONIX I.V. for this indication is supported by evidence from adequate and well-controlled studies of intravenous and oral pantoprazole sodium in adults and oral pantoprazole sodium in pediatric patients, with additional pharmacokinetic and safety data of intravenous pantoprazole in pediatric patients 1 year of age and older and oral pantoprazole in pediatric patients 3 months of age and older. Adverse reactions were generally similar to those reported in adults with intravenous or oral pantoprazole sodium [see Adverse Reactions (6.1) and Clinical Pharmacology (12.3)].

The safety and effectiveness of PROTONIX I.V. have not been established in patients less than 3 months of age for the treatment of GERD and a history of EE.

The safety and effectiveness of PROTONIX I.V. have not been established in pediatric patients for the treatment of pathological hypersecretory conditions including ZE syndrome.

Animal Toxicity Data

In neonatal/juvenile animals (rats and dogs) toxicities were similar to those observed in adult animals, including gastric alterations, decreases in red cell mass, increases in lipids, enzyme induction and hepatocellular hypertrophy. An increased incidence of eosinophilic chief cells in adult and neonatal/juvenile rats, and atrophy of chief cells in adult rats and in neonatal/juvenile dogs, was observed in the fundic mucosa of stomachs in repeated-dose studies. Full to partial recovery of these effects were noted in animals of both age groups following a recovery period.

8.5 Geriatric Use

Of 286 patients in clinical studies of intravenous pantoprazole sodium in patients with GERD and a history of EE, 86 (43%) were 65 years of age and over. No overall differences in safety or effectiveness were observed between these geriatric and younger adult patients, and other reported clinical experience with oral pantoprazole sodium has not identified differences in responses between geriatric and younger adult patients, but greater sensitivity of some older individuals cannot be ruled out.

No clinically meaningful differences in the pharmacokinetics of pantoprazole were observed in geriatric subjects compared to younger adult subjects [see Clinical Pharmacology (12.3)].

10 OVERDOSAGE

Experience in patients taking very high doses of pantoprazole (greater than 240 mg) is limited. Adverse reactions seen in spontaneous reports of overdose generally reflect the known safety profile of pantoprazole.

Pantoprazole is not removed by hemodialysis. In case of overdose, treatment should be symptomatic and supportive.

Single intravenous doses of pantoprazole at 378, 230, and 266 mg/kg (38, 46, and 177 times the recommended human dose based on body surface area) were lethal to mice, rats and dogs, respectively. The symptoms of acute toxicity were hypoactivity, ataxia, hunched sitting, limb-splay, lateral position, segregation, absence of ear reflex, and tremor.

11 DESCRIPTION

The active ingredient in PROTONIX® I.V. (pantoprazole sodium), a PPI, is a substituted benzimidazole, sodium 5-(difluoromethoxy)-2-[[(3,4-dimethoxy-2-pyridinyl)methyl] sulfinyl]-1H-benzimidazole, a compound that inhibits gastric acid secretion. Its empirical formula is C16H14F2N3NaO4S, with a molecular weight of 405.4. The structural formula is:

Pantoprazole sodium is a white to off-white crystalline powder and is racemic. Pantoprazole has weakly basic and acidic properties. Pantoprazole sodium is freely soluble in water, very slightly soluble in phosphate buffer at pH 7.4, and practically insoluble in n-hexane. The reconstituted solution of PROTONIX I.V. is in the pH range of 9.0 to 10.5.

PROTONIX I.V. is supplied for intravenous administration as a sterile, freeze-dried powder in a single-dose clear glass vial fitted with a rubber stopper and crimp seal. Each vial contains 40 mg pantoprazole (equivalent to 45.1 mg of pantoprazole sodium), edetate disodium (1 mg), and sodium hydroxide to adjust pH.

12 CLINICAL PHARMACOLOGY

12.1 Mechanism of Action

Pantoprazole is a PPI that suppresses the final step in gastric acid production by covalently binding to the (H^+, K^+)-ATPase enzyme system at the secretory surface of the gastric parietal cell. This effect leads to inhibition of both basal and stimulated gastric acid secretion irrespective of the stimulus. The binding to the (H^+, K^+)-ATPase results in a duration of antisecretory effect that persists longer than 24 hours for all doses tested (20 mg to 120 mg).

12.2 Pharmacodynamics

Antisecretory Activity

The magnitude and time course for inhibition of pentagastrin-stimulated acid output (PSAO) by single doses (20 to 120 mg) of PROTONIX I.V. were assessed in a single-dose, open-label, placebo-controlled, dose-response study. The results of this study are shown in Table 4. Healthy subjects received a continuous infusion for 25 hours of pentagastrin (PG) at 1 mcg/kg/h, a dose known to produce submaximal gastric acid secretion. The placebo group showed a sustained, continuous acid output for 25 hours, validating the reliability of the testing model. PROTONIX I.V. had an onset of antisecretory activity within 15 to 30 minutes of administration. Doses of 20 to 80 mg of PROTONIX I.V. substantially reduced the 24-hour cumulative PSAO in a dose-dependent manner, despite a short plasma elimination half-life. Complete suppression of PSAO was achieved with 80 mg within approximately 2 hours and no further significant suppression was seen with 120 mg. The duration of action of PROTONIX I.V. was 24 hours.

Table 4: Gastric Acid Output (mEq/hr, Mean ± SD) and Percent Inhibition [Compared to individual subject baseline prior to treatment with PROTONIX I.V.] (Mean ± SD) of Pentagastrin Stimulated Acid Output Over 24 Hours Following a Single Dose of PROTONIX I.V. [Inhibition of gastric acid output and the percent inhibition of stimulated acid output in response to PROTONIX I.V. may be higher after repeated doses.] in Healthy Subjects
 | ------2 hours------ |  | ------4 hours------ |  | ------12 hours------ |  | ------24 hours------
Treatment Dose | Acid Output | % Inhibition | Acid Output | % Inhibition | Acid Output | % Inhibition | Acid Output | % Inhibition
0 mg (Placebo, n=4) | 39 ± 21 | NA | 26 ± 14 | NA | 32 ± 20 | NA | 38 ± 24 | NA
20 mg (n=4–6) | 13 ± 18 | 47 ± 27 | 6 ± 8 | 83 ± 21 | 20 ± 20 | 54 ± 44 | 30 ± 23 | 45 ± 43
40 mg (n=8) | 5 ± 5 | 82 ± 11 | 4 ± 4 | 90 ± 11 | 11 ± 10 | 81 ± 13 | 16 ± 12 | 52 ± 36
80 mg (n=8) | 0.1 ± 0.2 | 96 ± 6 | 0.3 ± 0.4 | 99 ± 1 | 2 ± 2 | 90 ± 7 | 7 ± 4 | 63 ± 18
NA = not applicable.

In one study of gastric pH in healthy subjects, pantoprazole was administered orally (40 mg enteric coated tablets) or PROTONIX I.V. (40 mg) once daily for 5 days and pH was measured for 24 hours following the fifth dose. The outcome measure was median percent of time that pH was ≥4 and the results were similar for intravenous and oral medications; however, the clinical significance of this parameter is unknown.

Serum Gastrin Effects

Serum gastrin concentrations were assessed in two placebo-controlled studies.

In a 5-day study of oral pantoprazole with 40 and 60 mg doses in healthy subjects, following the last dose on day 5, median 24-hour serum gastrin concentrations were elevated by 3- to 4-fold compared to placebo in both 40 and 60 mg dose groups. However, by 24 hours following the last dose, median serum gastrin concentrations for both groups returned to normal levels.

In another placebo-controlled, 7-day study of 40 mg intravenous or oral pantoprazole in patients with GERD and a history of EE, the mean serum gastrin concentration increased approximately 50% from baseline and as compared with placebo, but remained within the normal range.

During 6 days of repeated administration of PROTONIX I.V. in patients with ZE Syndrome, consistent changes of serum gastrin concentrations from baseline were not observed.

Enterochromaffin-Like (ECL) Cell Effects

There are no data available on the effects of intravenous pantoprazole sodium on ECL cells.

In a nonclinical study in Sprague-Dawley rats, lifetime exposure (24 months) to oral pantoprazole at doses of 0.5 to 200 mg/kg/day resulted in dose-related increases in gastric ECL-cell proliferation and gastric neuroendocrine (NE)-cell tumors. Gastric NE-cell tumors in rats may result from chronic elevation of serum gastrin concentrations. The high density of ECL cells in the rat stomach makes this species highly susceptible to the proliferative effects of elevated gastrin concentrations produced by PPIs. However, there were no observed elevations in serum gastrin following the administration of oral pantoprazole at a dose of 0.5 mg/kg/day. In a separate study, a gastric NE-cell tumor without concomitant ECL-cell proliferative changes was observed in 1 female rat following 12 months of dosing with oral pantoprazole at 5 mg/kg/day and a 9 month off-dose recovery [see Nonclinical Toxicology (13.1)].

Endocrine Effects

In a clinical pharmacology study, pantoprazole 40 mg given orally once daily for 2 weeks had no effect on the levels of the following hormones: cortisol, testosterone, triiodothyronine (T3), thyroxine (T4), thyroid-stimulating hormone, thyronine-binding protein, parathyroid hormone, insulin, glucagon, renin, aldosterone, follicle-stimulating hormone, luteinizing hormone, prolactin and growth hormone.

In a 1-year study of GERD patients treated with pantoprazole 40 mg or 20 mg, there were no changes from baseline in overall levels of T3, T4, and TSH.

12.3 Pharmacokinetics

Pantoprazole peak serum concentration (Cmax) and area under the serum concentration-time curve (AUC) increase in a manner proportional to intravenous doses from 10 mg to 80 mg. Pantoprazole does not accumulate and its pharmacokinetics are unaltered with multiple daily dosing. Following the administration of PROTONIX I.V., the serum concentration of pantoprazole declines biexponentially with a terminal elimination half-life of approximately one hour. In CYP2C19 extensive metabolizers [see Clinical Pharmacology (12.5)] with normal liver function receiving a 40 mg dose of PROTONIX I.V. by constant rate over 15 minutes, the peak concentration (Cmax) is 5.52 ±1.42 mcg/mL and the total area under the plasma concentration versus time curve (AUC) is 5.4 ±1.5 mcg• hr/mL. The total clearance is 7.6 to 14 L/h.

Distribution

The apparent volume of distribution of pantoprazole is approximately 11 to 23.6 L, distributing mainly in extracellular fluid. The serum protein binding of pantoprazole is about 98%, primarily to albumin.

Elimination

Metabolism

Pantoprazole is extensively metabolized in the liver through the cytochrome P450 (CYP) system. Pantoprazole metabolism is independent of the route of administration (intravenous or oral). The main metabolic pathway is demethylation, by CYP2C19, with subsequent sulfation; other metabolic pathways include oxidation by CYP3A4. There is no evidence that any of the pantoprazole metabolites have significant pharmacologic activity. CYP2C19 displays a known genetic polymorphism due to its deficiency in some sub-populations (e.g., 3% of Whites and African-Americans and 17 to 23% of Asians). Although these sub-populations of slow pantoprazole metabolizers have elimination half-life values from 3.5 to 10 hours, they still have minimal accumulation (23% or less) with once daily dosing.

Excretion

After administration of a single intravenous dose of ^14C-labeled pantoprazole sodium to healthy, extensive CYP2C19 metabolizers, approximately 71% of the dose was excreted in the urine with 18% excreted in the feces through biliary excretion. There was no renal excretion of unchanged pantoprazole.

Specific Populations

Geriatric Patients

After repeated intravenous administration in elderly subjects (65 to 76 years of age), the AUC and elimination half-life values of pantoprazole were similar to those observed in younger subjects.

Pediatric Patients

The pharmacokinetics of pantoprazole were studied in 40 pediatric patients 1 to less than 16 years of age in three open-label clinical trials in pediatric patients with GERD following intravenous administration and 180 pediatric patients from birth to 16 years of age in four randomized, open-label clinical studies in pediatric patients with GERD following oral administration.

Population PK analyses predicted the following dosage regimens would achieve comparable steady-state plasma exposures (AUC0-24) to those observed in adult patients administered 40 mg of PROTONIX I.V. once daily: 0.8 mg/kg once daily for pediatric patients 3 months to less than 1 year, 10 mg once daily for pediatric patients 1 year to 17 years with body weight less than 15 kg, 20 mg once daily for pediatric patients 1 year to 17 years with body weight greater than 15 kg but less than 40 kg, and 40 mg once daily for pediatric patients 1 year to 17 years with body weight of 40 kg and greater. The pharmacokinetics of pantoprazole following intravenous administration in pediatric patients less than 3 months of age have not been characterized.

Male and Female Patients

After oral administration there was a modest increase in the AUC and Cmax of pantoprazole in women compared to men. However, weight-normalized clearance values are similar in women and men.

Patients with Renal Impairment

In patients with severe renal impairment, pharmacokinetic parameters for pantoprazole were similar to those of healthy subjects.

Patients with Hepatic Impairment

In patients with mild to severe hepatic impairment (Child-Pugh Class A to C), maximum pantoprazole concentrations increased only slightly (1.5-fold) relative to healthy subjects when pantoprazole sodium was administered orally. Although serum half-life values increased to 7 to 9 hours and AUC values increased by 5- to 7-fold in hepatic-impaired patients, these increases were no greater than those observed in CYP2C19 poor metabolizers, where no dosage adjustment is warranted. These pharmacokinetic changes in hepatic-impaired patients result in minimal drug accumulation following once daily, multiple-dose administration. Oral pantoprazole doses higher than 40 mg per day have not been studied in hepatically impaired patients.

Drug Interaction Studies

Effect of Other Drugs on Pantoprazole

Pantoprazole is metabolized mainly by CYP2C19 and to minor extents by CYPs 3A4, 2D6 and 2C9.

In in vivo drug-drug interaction studies with CYP2C19 substrates (diazepam [also a CYP3A4 substrate] and phenytoin [also a CYP3A4 inducer]), nifedipine, midazolam, and clarithromycin (CYP3A4 substrates), metoprolol (a CYP2D6 substrate), diclofenac, naproxen and piroxicam (CYP2C9 substrates) and theophylline (a CYP1A2 substrate) in healthy subjects, the pharmacokinetics of pantoprazole were not significantly altered.

Effect of Pantoprazole on Other Drugs

Clopidogrel

Clopidogrel is metabolized to its active metabolite in part by CYP2C19. In a crossover clinical study, 66 healthy subjects were administered clopidogrel (300 mg loading dose followed by 75 mg per day) alone and with oral pantoprazole (80 mg at the same time as clopidogrel) for 5 days. On Day 5, the mean AUC of the active metabolite of clopidogrel was reduced by approximately 14% (geometric mean ratio was 86%, with 90% CI of 79 to 93%) when pantoprazole sodium was coadministered with clopidogrel as compared to clopidogrel administered alone. Pharmacodynamic parameters were also measured and demonstrated that the change in inhibition of platelet aggregation (induced by 5 micromolar ADP) was correlated with the change in the exposure to clopidogrel active metabolite. The clinical significance of this finding is not clear.

Mycophenolate Mofetil (MMF)

Administration of oral pantoprazole 40 mg twice daily for 4 days and a single 1000 mg dose of MMF approximately one hour after the last dose of pantoprazole to 12 healthy subjects in a cross-over study resulted in a 57% reduction in the Cmax and 27% reduction in the AUC of MPA. Transplant patients receiving approximately 2000 mg per day of MMF (n=12) were compared to transplant patients receiving approximately the same dose of MMF and oral pantoprazole 40 mg per day (n=21). There was a 78% reduction in the Cmax and a 45% reduction in the AUC of MPA in patients receiving both pantoprazole and MMF [see Drug Interactions (7)].

Other Drugs

In vivo studies also suggest that pantoprazole does not significantly affect the kinetics of other drugs (theophylline, diazepam [and its active metabolite, desmethyldiazepam], phenytoin, metoprolol, nifedipine, carbamazepine, midazolam, clarithromycin, diclofenac, naproxen, piroxicam and oral contraceptives [levonorgestrel/ethinyl estradiol]). In other in vivo studies, digoxin, ethanol, glyburide, antipyrine, caffeine, metronidazole, and amoxicillin had no clinically relevant interactions with pantoprazole.

Although no significant drug-drug interactions have been observed in clinical studies, the potential for significant drug-drug interactions with more than once daily dosing with high doses of pantoprazole has not been studied in poor metabolizers or individuals who are hepatically impaired.

Antacids

There was also no interaction with concomitantly administered antacids.

12.5 Pharmacogenomics

CYP2C19 displays a known genetic polymorphism due to its deficiency in some subpopulations (e.g., approximately 3% of Whites and African-Americans and 17% to 23% of Asians are poor metabolizers). Although these subpopulations of pantoprazole poor metabolizers have elimination half-life values of 3.5 to 10 hours in adults, they still have minimal accumulation (23% or less) with once daily dosing. For adult patients who are CYP2C19 poor metabolizers, no dosage adjustment is needed.

Similar to adults, pediatric patients who have the poor metabolizer genotype of CYP2C19 (CYP2C19 *2/*2) exhibited greater than a 6-fold increase in AUC compared to pediatric extensive (CYP2C19 *1/*1) and intermediate (CYP2C19 *1/*x) metabolizers. Poor metabolizers exhibited approximately 10-fold lower apparent oral clearance compared to extensive metabolizers.

13 NONCLINICAL TOXICOLOGY

13.1 Carcinogenesis, Mutagenesis, Impairment of Fertility

In a 24-month carcinogenicity study, Sprague-Dawley rats were treated orally with pantoprazole doses of 0.5 to 200 mg/kg/day, about 0.1 to 40 times the exposure on a body surface area basis of a 50-kg person dosed at 40 mg/day. In the gastric fundus, treatment with 0.5 to 200 mg/kg/day produced enterochromaffin-like (ECL) cell hyperplasia and benign and malignant neuroendocrine cell tumors in a dose-related manner. In the forestomach, treatment with 50 and 200 mg/kg/day (about 10 and 40 times the recommended human dose on a body surface area basis) produced benign squamous cell papillomas and malignant squamous cell carcinomas. Rare gastrointestinal tumors associated with pantoprazole treatment included an adenocarcinoma of the duodenum with 50 mg/kg/day and benign polyps and adenocarcinomas of the gastric fundus with 200 mg/kg/day. In the liver, treatment with 0.5 to 200 mg/kg/day produced dose-related increases in the incidences of hepatocellular adenomas and carcinomas. In the thyroid gland, treatment with 200 mg/kg/day produced increased incidences of follicular cell adenomas and carcinomas for both male and female rats.

In a 24-month carcinogenicity study, Fischer 344 rats were treated orally with pantoprazole doses of 5 to 50 mg/kg/day, approximately 1 to 10 times the recommended human dose based on body surface area. In the gastric fundus, treatment with 5 to 50 mg/kg/day produced enterochromaffin-like (ECL) cell hyperplasia and benign and malignant neuroendocrine cell tumors. Dose selection for this study may not have been adequate to comprehensively evaluate the carcinogenic potential of pantoprazole.

In a 24-month carcinogenicity study, B6C3F1 mice were treated orally with pantoprazole doses of 5 to 150 mg/kg/day, 0.5 to 15 times the recommended human dose based on body surface area. In the liver, treatment with 150 mg/kg/day produced increased incidences of hepatocellular adenomas and carcinomas in female mice. Treatment with 5 to 150 mg/kg/day also produced gastric fundic ECL cell hyperplasia.

A 26-week p53 +/- transgenic mouse carcinogenicity study was not positive.

Pantoprazole was positive in the in vitro human lymphocyte chromosomal aberration assays, in one of two mouse micronucleus tests for clastogenic effects, and in the in vitro Chinese hamster ovarian cell/HGPRT forward mutation assay for mutagenic effects. Equivocal results were observed in the in vivo rat liver DNA covalent binding assay. Pantoprazole was negative in the in vitro Ames mutation assay, the in vitro unscheduled DNA synthesis (UDS) assay with rat hepatocytes, the in vitro AS52/GPT mammalian cell-forward gene mutation assay, the in vitro thymidine kinase mutation test with mouse lymphoma L5178Y cells, and the in vivo rat bone marrow cell chromosomal aberration assay.

There were no effects on fertility or reproductive performance when pantoprazole was given at oral doses up to 500 mg/kg/day in male rats (98 times the recommended human dose based on body surface area) and 450 mg/kg/day in female rats (88 times the recommended human dose based on body surface area).

14 CLINICAL STUDIES

14.1 Gastroesophageal Reflux Disease (GERD) Associated with a History of Erosive Esophagitis (EE)

A multicenter, double-blind, two-period placebo-controlled study was conducted to assess the ability of PROTONIX® I.V. to maintain gastric acid suppression in patients switched from pantoprazole sodium delayed-release tablets to PROTONIX I.V. GERD patients (n=65, 26 to 64 years; 35 female; 9 Black, 11 Hispanic, 44 White, 1 other) with a history of EE were randomized to receive either 20 or 40 mg of oral pantoprazole once per day for 10 days (period 1), and then were switched in period 2 to either daily PROTONIX I.V. or placebo for 7 days, matching their respective dose level from period 1. Patients were administered all test medication with a light meal. Maximum acid output (MAO) and basal acid output (BAO) were determined 24 hours following the last day of oral medication (day 10), the first day (day 1) of intravenous administration and the last day of intravenous administration (day 7). MAO was estimated from a 1 hour continuous collection of gastric contents following subcutaneous injection of 6.0 mcg/kg of pentagastrin.

This study demonstrated that, after 10 days of repeated oral administration followed by 7 days of intravenous administration, the oral and intravenous dosage forms of pantoprazole 40 mg are similar in their ability to suppress MAO and BAO in patients with GERD and a history of EE (see Table 5). Also, patients on oral PROTONIX who were switched to intravenous placebo experienced a significant increase in acid output within 48 hours of their last oral dose (see Table 5). However, at 48 hours after their last oral dose, patients treated with PROTONIX I.V. had a significantly lower mean basal acid output (see Table 5) than those treated with placebo.

Table 5: Antisecretory Effects (mEq/h) of 40 mg PROTONIX I.V. and 40 mg Pantoprazole Delayed-Release Tablets in GERD Patients with a History of EE
Parameter | Pantoprazole Delayed-Release Tablets DAY 10 | PROTONIX I.V. DAY 7 | Intravenous Placebo DAY 7
Mean maximum acid output | 6.49 n=30 | 6.62 n=23 | 29.19 [p<0.0001 Significantly different from PROTONIX I.V.] n=7
Mean basal acid output | 0.80 n=30 | 0.53 n=23 | 4.14 n=7

To evaluate the effectiveness of PROTONIX I.V. as an initial treatment to suppress gastric acid secretion, two studies were conducted.

Study 1 was a multicenter, double-blind, placebo-controlled, study of the pharmacodynamic effects of PROTONIX I.V. and pantoprazole sodium delayed-release tablets. Patients with GERD and a history of EE (n=78, 20 to 67 years; 39 females; 7 Black, 19 Hispanic, 52 White) were randomized to receive either 40 mg PROTONIX I.V., 40 mg pantoprazole sodium delayed-release tablets, or placebo once daily for 7 days. Following an overnight fast, test medication was administered and patients were given a light meal within 15 minutes. MAO and BAO were determined 24 hours following the last day of study medication. MAO was estimated from a 1 hour continuous collection of gastric contents following subcutaneous injection of 6.0 mcg/kg of pentagastrin to stimulate acid secretion. This study demonstrated that, after treatment for 7 days, patients treated with PROTONIX I.V. had a significantly lower MAO and BAO than those treated with placebo (p<0.001), and results were comparable to those of patients treated with pantoprazole sodium delayed-release tablets (see Table 6).

Table 6: Antisecretory Effects (mEq/h) of Initial Treatment with 40 mg PROTONIX I.V. and 40 mg Pantoprazole Delayed-Release Tablets in GERD Patients with a History of EE
Parameter | PROTONIX I.V. DAY 7 | Pantoprazole Delayed-Release Tablets DAY 7 | Placebo DAY 7
Maximum acid output (mean ± SD) | 8.4 ± 5.9 n=25 | 6.3 ± 6.6 n=22 | 20.9 ± 14.5 [p<0.001 Significantly different from PROTONIX I.V.] n=24
Basal acid output (mean ± SD) | 0.4 ± 0.5 n=25 | 0.6 ± 0.8 n=22 | 2.8 ± 3.0 n=23

Study 2 was a single-center, double-blind, parallel-group study to compare the clinical effects of PROTONIX I.V. and pantoprazole sodium delayed-release tablets. Patients (n=45, median age 56 years, 21 males and 24 females) with acute endoscopically proven reflux esophagitis (Savary/Miller Stage II or III) with at least 1 of 3 symptoms typical for reflux esophagitis (acid eructation, heartburn, or pain on swallowing) were randomized to receive either 40 mg PROTONIX I.V. or 40 mg pantoprazole sodium delayed-release tablets once daily for 5 days. After the initial 5 days, all patients were treated with 40 mg oral pantoprazole daily to complete a total of 8 weeks of treatment. Symptom relief was assessed by calculating the daily mean of the sums of the average scores for these 3 symptoms and the daily mean of the average score for each of the symptoms separately. There was no significant difference in symptom relief between PROTONIX I.V. and pantoprazole sodium delayed-release tablets within the first 5 days. A repeat endoscopy after 8 weeks of treatment revealed that 20 out of 23 (87%) patients treated with PROTONIX I.V. plus pantoprazole sodium delayed-release tablets and 19 out of 22 (86%) of the patients treated with pantoprazole sodium delayed-release tablets had endoscopically proven healing of their esophageal lesions.

Data comparing PROTONIX I.V. to other PPIs (oral or intravenous) or H2-receptor antagonists (oral or intravenous) are limited, and therefore, are inadequate to support any conclusions regarding comparative efficacy.

14.2 Pathological Hypersecretion Associated with Zollinger-Ellison Syndrome

Two studies measured the pharmacodynamic effects of 6 day treatment with PROTONIX I.V. in patients with ZE Syndrome (with and without multiple endocrine neoplasia type I). In one of these studies, an initial treatment with PROTONIX I.V. in 21 patients (29 to 75 years; 8 female; 4 Black, 1 Hispanic, 16 White) reduced acid output to the target level (10 mEq/h or less) and significantly reduced H^+ concentration and the volume of gastric secretions; target levels were achieved within 45 minutes of drug administration.

In the other study of 14 patients (38 to 67 years; 5 female; 2 Black, 12 White) with ZE Syndrome, treatment was switched from an oral PPI to PROTONIX I.V. PROTONIX I.V. maintained or improved control of gastric acid secretion.

In both studies, total doses of 160 or 240 mg per day of PROTONIX I.V., administered in divided doses, maintained basal acid secretion below target levels in all patients. Target levels were 10 mEq/h in patients without prior gastric surgery, and 5 mEq/h in all patients with prior gastric acid-reducing surgery. Once gastric acid secretion was controlled, there was no evidence of tolerance during this 7 day study. Basal acid secretion was maintained below target levels for at least 24 hours in all patients and through the end of treatment in these studies (3 to 7 days) in all but 1 patient who required a dose adjustment guided by acid output measurements until acid control was achieved. In both studies, doses were adjusted to the individual patient need, but gastric acid secretion was controlled in greater than 80% of patients by a starting regimen of 80 mg every 12 hours.

16 HOW SUPPLIED/STORAGE AND HANDLING

PROTONIX® I.V. (pantoprazole sodium) is supplied in a single-dose vial as a white to off-white freeze-dried powder for reconstitution and dilution containing 40 mg of pantoprazole.

PROTONIX I.V. is available as follows:

NDC Number | Strength | Package Size
NDC 0008-4001-10 | 40 mg/vial pantoprazole | 10 vials
NDC 0008-4001-25 | 40 mg/vial pantoprazole | 25 vials

Storage and Handling

Store PROTONIX I.V. at 20° to 25°C (68° to 77°F); excursions permitted to 15° to 30°C (59° to 86°F) [see USP Controlled Room Temperature].

Protect from light.

17 PATIENT COUNSELING INFORMATION

Adverse Reactions

Advise patients to report to their healthcare provider if they experience any signs or symptoms consistent with:

- Injection Site Reactions [see Warnings and Precautions (5.2)]
- Potential for Exacerbation of Zinc Deficiency [see Warnings and Precautions (5.3)]
- Acute Tubulointerstitial Nephritis [see Contraindications (4) and Warnings and Precautions (5.4)]
- Clostridioides difficile-Associated Diarrhea [see Warnings and Precautions (5.5)]
- Bone Fracture [see Warnings and Precautions (5.6)]
- Severe Cutaneous Adverse Reactions [see Warnings and Precautions (5.7)]
- Cutaneous and Systemic Lupus Erythematosus [see Warnings and Precautions (5.8)]
- Hepatic Effects [see Warnings and Precautions (5.9)]
- Hypomagnesemia and Mineral Metabolism [see Warnings and Precautions (5.10)]

Drug Interactions

Advise patients to report to their healthcare provider before they start treatment with any of the following:

- rilpivirine-containing products [Contraindications (4)]
- high dose methotrexate [Warnings and Precautions (5.14)].

Pregnancy

Advise a pregnant woman of the potential risk to a fetus. Advise females of reproductive potential to inform their healthcare provider of a known or suspected pregnancy [see Use in Specific Populations (8.1)].

This product's labeling may have been updated. For the most recent prescribing information, please visit www.pfizer.com.

Distributed by
Wyeth Pharmaceuticals LLC
A subsidiary of Pfizer Inc
Philadelphia, PA 19101

under license from
Takeda GmbH
D78467 Konstanz, Germany

PREMIERProRx® is a registered trademark of Premier Healthcare Alliance, L.P., used under license.

LAB-0661-15.0

PRINCIPAL DISPLAY PANEL - 40 mg Vial Label

NDC 0008-4001-01

PROTONIX® I.V.
(pantoprazole sodium)
for Injection

40 mg/vial

Sterile
For Intravenous Use
Single-dose vial

Rx only

PREMIERProRx®

PRINCIPAL DISPLAY PANEL - 40 mg Vial Carton

NDC 0008-4001-01
Rx only

PROTONIX® I.V.
(pantoprazole sodium)
for Injection

40 mg/vial

Sterile
For Intravenous Use
Single-dose vial

Contains 1 mg edetate disodium
No filter required

PREMIERProRx®

PRINCIPAL DISPLAY PANEL - 10 Vial Carton Package Label

Each vial contains:
Pantoprazole
40 mg
(equivalent to 45.1 mg of pantoprazole
sodium)
Contains 1 mg edetate disodium
Store at 20°-25°C (68°-77°F);
excursions permitted to 15°-30°C
(59°-86°F). [See USP Controlled Room
Temperature].
Protect vials from light; use of vial
carton is recommended.
Dist. by Wyeth Pharmaceuticals LLC
A subsidiary of Pfizer Inc
Philadelphia, PA 19101
Under license from Takeda GmbH
D78467 Konstanz, Germany
PREMIERProRx® is a registered trademark
of Premier Healthcare Alliance, L.P.,
used under license.
MADE IN FRANCE
R04/0924/6171043

1 Bundle of 10 unit cartons
NDC 0008-4001-10

PROTONIX® I.V.
(pantoprazole sodium) for Injection

40 mg/vial

Sterile
For Intravenous Use
Single-dose vial

PREMIERProRx®

Rx only

LOT

EXP

SN

GTIN: 00300084001109

PRINCIPAL DISPLAY PANEL - 25 Vial Carton Package

NDC 0008-4001-25
Contains 25 of NDC 0008-4001-01
Rx only

25 x 40 mg Vials

PROTONIX® I.V.
(pantoprazole sodium)
for Injection

40 mg/vial

Sterile
For Intravenous Use
Single-dose vial

PREMIERProRx®